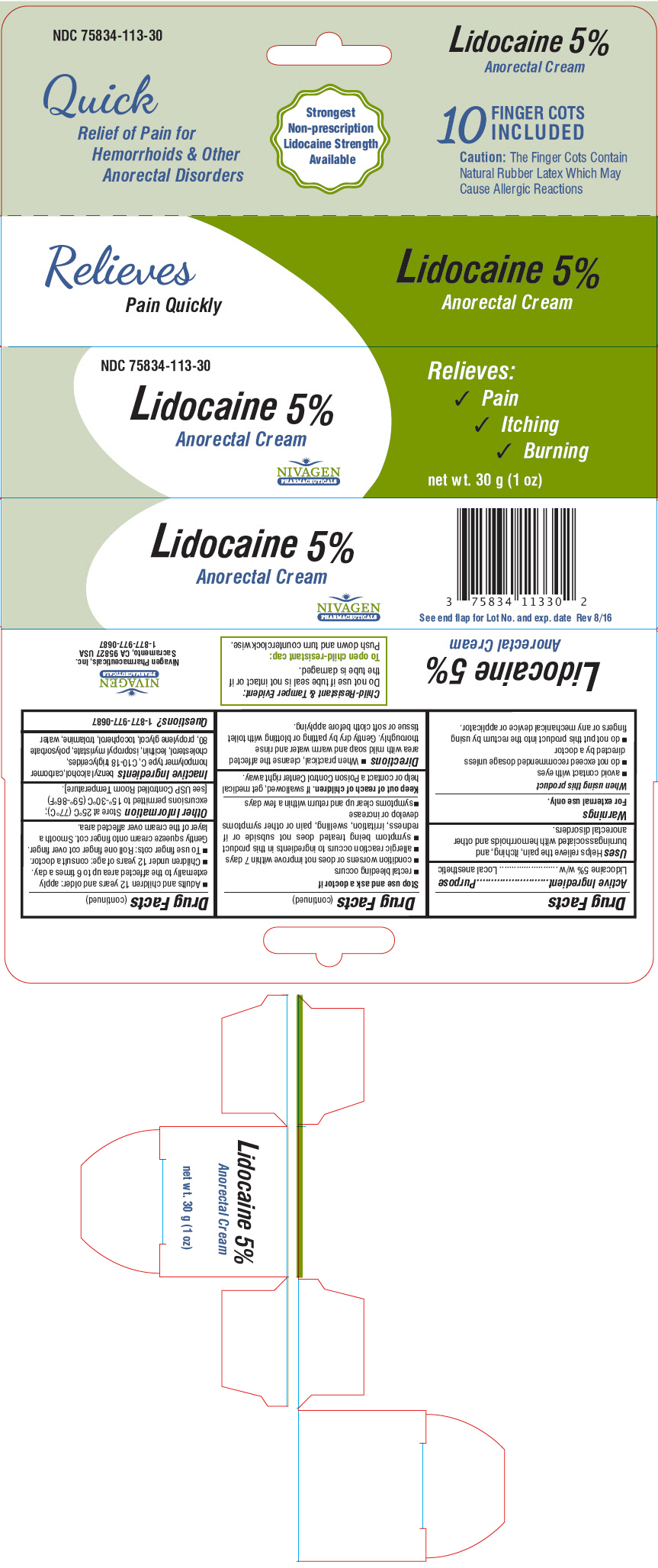 DRUG LABEL: Lidocaine
NDC: 75834-113 | Form: CREAM
Manufacturer: Nivagen Pharmaceuticals, Inc.
Category: otc | Type: HUMAN OTC DRUG LABEL
Date: 20200116

ACTIVE INGREDIENTS: Lidocaine 50 mg/1 g
INACTIVE INGREDIENTS: BENZYL ALCOHOL; CARBOMER HOMOPOLYMER TYPE C (ALLYL PENTAERYTHRITOL CROSSLINKED); MEDIUM-CHAIN TRIGLYCERIDES; CHOLESTEROL; LECITHIN, SOYBEAN; ISOPROPYL MYRISTATE; POLYSORBATE 80; PROPYLENE GLYCOL; TOCOPHEROL; TROLAMINE; WATER

Lidocaine 5%

Drug Facts

Active Ingredient

Lidocaine 5% w/w

Purpose

Local anesthetic

Uses

Helps relieve the pain, itching, and burningassociated with hemorrhoids and other anorectal disorders.

Warnings

For external use only.

When using this product

- avoid contact with eyes
- do not exceed recommended dosage unless directed by a doctor
- do not put this product into the rectum by using fingers or any mechanical device or applicator.

Stop use and ask a doctor if

- rectal bleeding occurs
- condition worsens or does not improve within 7 days
- allergic reaction occurs to ingredients in this product
- symptom being treated does not subside or if redness, irritation, swelling, pain or other symptoms develop or increase
- symptoms clear up and return within a few days

Keep out of reach of children. If swallowed, get medical help or contact a Poison Control Center right away.

Directions

- When practical, cleanse the affected area with mild soap and warm water and rinse thoroughly. Gently dry by patting or blotting with toilet tissue or soft cloth before applying.
- Adults and children 12 years and older: apply externally to the affected area up to 6 times a day.
- Children under 12 years of age: consult a doctor.
- To use finger cots: Roll one finger cot over finger. Gently squeeze cream onto finger cot. Smooth a layer of the cream over affected area.

Other Information

Store at 25°C (77°C); excursions permitted to 15°-30°C (59°-86°F) [see USP Controlled Room Temperature].

Inactive Ingredients

benzyl alcohol,carbomer hompolymer type C, C10-18 triglycerides, cholesterol, lecithin, isopropyl myristate, polysorbate 80, propylene glycol, tocopherol, trolamine, water

Questions?

1-877-977-0687

PRINCIPAL DISPLAY PANEL - 30 g Tube Carton

NDC 75834-113-30

Lidocaine 5%
Anorectal Cream

Relieves:

✓ Pain
✓ Itching
✓ Burning

NIVAGEN
PHARMACEUTICALS

net wt. 30 g (1 oz)